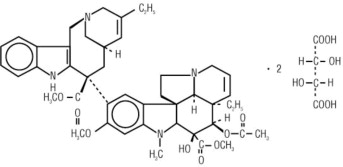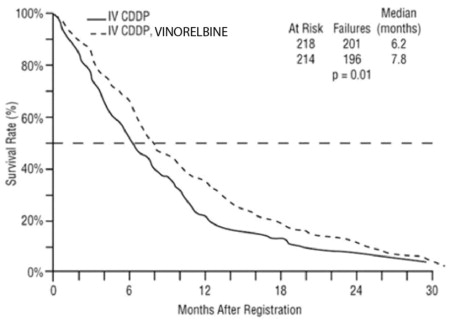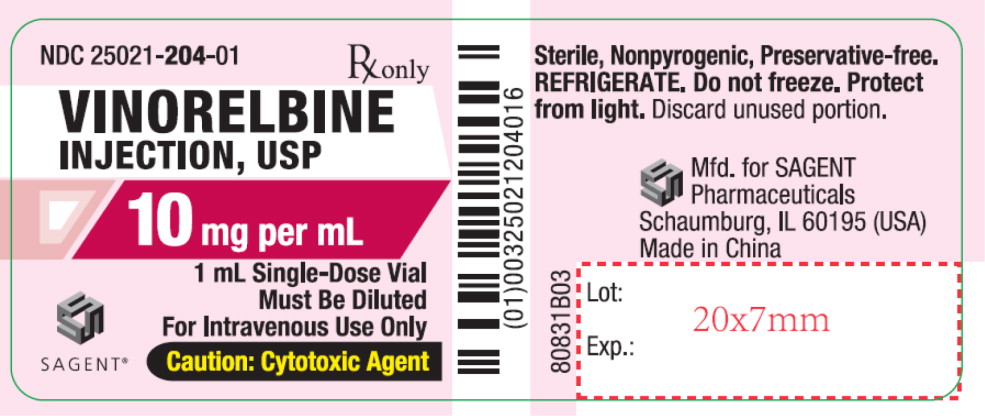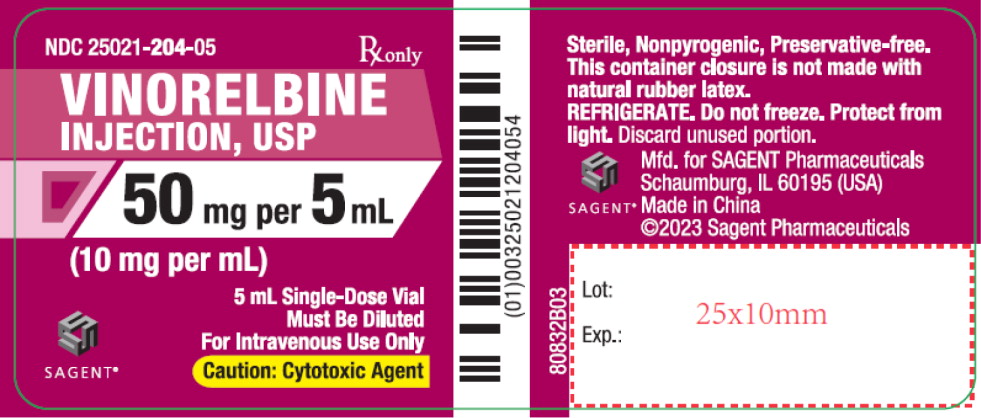 DRUG LABEL: Vinorelbine
NDC: 25021-204 | Form: INJECTION, SOLUTION
Manufacturer: Sagent Pharmaceuticals
Category: prescription | Type: HUMAN PRESCRIPTION DRUG LABEL
Date: 20240816

ACTIVE INGREDIENTS: vinorelbine tartrate 10 mg/1 mL
INACTIVE INGREDIENTS: water

HIGHLIGHTS OF PRESCRIBING INFORMATION

These highlights do not include all the information needed to use VINORELBINE INJECTION safely and effectively. See full prescribing information for VINORELBINE INJECTION.
VINORELBINE injection, for intravenous use
Initial U.S. Approval: 1994

WARNING: MYELOSUPPRESSION

See full prescribing information for complete boxed warning.

- Severe myelosuppression resulting in serious infection, septic shock, and death can occur (5.1).
- Decrease the dose or withhold vinorelbine in accord with recommended dose modifications (2.2).

1 INDICATIONS AND USAGE

Vinorelbine Injection is a vinca alkaloid indicated:

- In combination with cisplatin for first-line treatment of patients with locally advanced or metastatic non-small cell lung cancer (NSCLC) (1)
- As a single agent for first-line treatment of patients with metastatic NSCLC (1)

2 DOSAGE AND ADMINISTRATION

- In combination with cisplatin: 25 to 30 mg/m^2 as an intravenous injection or infusion once weekly (2.1)
- Single agent: 30 mg/m^2 as intravenously once a week (2.1)
- Adjust dose in patients with decreased neutrophil counts or elevated serum total bilirubin (2.2)

3 DOSAGE FORMS AND STRENGTHS

- Vinorelbine Injection: 10 mg per 1 mL and 50 mg per 5 mL in single-dose vial (3)

4 CONTRAINDICATIONS

None

5 WARNINGS AND PRECAUTIONS

- Hepatic Toxicity: Monitor hepatic function prior to initiation and during treatment (5.2)
- Severe constipation and bowel obstruction, including necrosis and perforation, occur. Institute a prophylactic bowel regimen to mitigate potential constipation, bowel obstruction and/or paralytic ileus (5.3)
- Extravasation can result in severe tissue injury, local tissue necrosis and/or thrombophlebitis. Immediately stop vinorelbine and institute recommended management procedures (5.4)
- Neurologic Toxicity: Severe sensory and motor neuropathies occur. Monitor patients for new or worsening signs and symptoms of neuropathy. Discontinue for Grade 2 or greater neuropathy (5.5)
- Pulmonary toxicity and respiratory failure occur. Interrupt vinorelbine in patients who develop unexplained dyspnea or have any evidence of pulmonary toxicity. Permanently discontinue for confirmed interstitial pneumonitis or ARDS (5.6)
- Embryo-Fetal Toxicity: Can cause fetal harm. Advise females of reproductive potential of potential risk to the fetus and to use effective contraception (5.7, 8.1, 8.3)

6 ADVERSE REACTIONS

Most common adverse reactions (incidence ≥ 20%) are leukopenia, neutropenia, anemia, increased aspartate aminotransferase, nausea, vomiting, constipation, asthenia, injection site reaction and peripheral neuropathy (6.1)

To report SUSPECTED ADVERSE REACTIONS, contact Sagent Pharmaceuticals at 1-866-625-1618 or FDA at 1-800-FDA-1088 or www.fda.gov/medwatch.

7 DRUG INTERACTIONS

- Inhibitors of CYP3A4: May cause earlier onset and/or increased severity of adverse reactions (7.1)

8 USE IN SPECIFIC POPULATIONS

- Lactation: Advise not to breastfeed (8.2)

FULL PRESCRIBING INFORMATION

WARNING: MYELOSUPPRESSION

- Severe myelosuppression resulting in serious infection, septic shock, hospitalization and death can occur [see Warnings and Precautions (5.1)].
- Decrease the dose or withhold vinorelbine in accord with recommended dose modifications [see Dosage and Administration (2.2)].

1 INDICATIONS AND USAGE

Vinorelbine Injection is indicated:

- In combination with cisplatin for first-line treatment of patients with locally advanced or metastatic non-small cell lung cancer (NSCLC)
- As a single agent for the treatment of patients with metastatic NSCLC

2 DOSAGE AND ADMINISTRATION

2.1 Recommended Dosage

In Combination with Cisplatin 100 mg/m^2

- The recommended dosage of Vinorelbine Injection is 25 mg/m^2 administered as an intravenous injection or infusion over 6 to 10 minutes on Days 1, 8, 15 and 22 of a 28-day cycle in combination with cisplatin 100 mg/m^2 on Day 1 only of each 28-day cycle.

In Combination with Cisplatin 120 mg/m^2

- The recommended dosage of Vinorelbine Injection is 30 mg/m^2 administered as an intravenous injection or infusion over 6 to 10 minutes once a week in combination with cisplatin 120 mg/m^2 on Days 1 and 29, then every 6 weeks.

Single Agent

- The recommended dosage of Vinorelbine Injection is 30 mg/m^2 administered intravenously over 6 to 10 minutes once a week.

2.2 Dosage Modifications

Myelosuppression

Hold or decrease the dose of Vinorelbine Injection in patients with decreased neutrophil counts according to the following schema [see Warnings and Precautions (5.1)]:

Neutrophils on Day of Treatment (cells/mm^3) | Percentage of Starting Dose of Vinorelbine Injection
≥ 1,500 | 100%
1,000 to 1,499 | 50%
< 1,000 | Do not administer Vinorelbine Injection. Repeat neutrophil count in one week. If three consecutive weekly doses are held because neutrophil count is < 1,000 cells/mm^3, discontinue Vinorelbine Injection
Note: For patients who experience fever and/or sepsis while neutrophil count is < 1,500 cells/mm^3 or had 2 consecutive weekly doses held due to neutropenia, subsequent doses of Vinorelbine Injection should be:
> 1,500 | 75%
1,000 to 1,499 | 37.5%
< 1,000 | Do not administer Vinorelbine Injection. Repeat neutrophil count in one week.

Hepatic Impairment/Toxicity

Reduce Vinorelbine Injection dose in patients with elevated serum total bilirubin concentration according to the following schema [see Warnings and Precautions (5.2) and Use in Specific Populations (8.6)]:

Serum Total Bilirubin Concentration (mg/dl) | Percentage of Starting Dose of Vinorelbine Injection
≤ 2.0 | 100%
2.1 to 3.0 | 50%
> 3.0 | 25%

Concurrent Myelosuppression and Hepatic Impairment/Toxicity

In patients with both myelosuppression and hepatic impairment/toxicity, administer the lower of the doses based on the corresponding starting dose of Vinorelbine Injection determined from the above schemas.

Neurologic Toxicity

Discontinue Vinorelbine Injection for Common Terminology Criteria for Adverse Events (CTCAE) Grade 2 or higher peripheral neuropathy or autonomic neuropathy causing constipation [see Warnings and Precautions (5.5)].

2.3 Preparation and Administration

Preparation

Dilute Vinorelbine Injection in an intravenous bag to a concentration between 0.5 mg/mL and 2 mg/mL. Use one of the following recommended solutions for dilution:

- 5% Dextrose Injection, USP
- 0.9% Sodium Chloride Injection, USP
- 0.45% Sodium Chloride Injection, USP
- 5% Dextrose and 0.45% Sodium Chloride Injection, USP
- Ringer's Injection, USP
- Lactated Ringer's Injection, USP

Stability and Storage Conditions of Diluted Solutions

Diluted Vinorelbine Injection may be used for up to 24 hours under normal room light when stored in polyvinyl chloride bags at 5° to 30°C (41° to 86°F).

Administration

Administer diluted Vinorelbine Injection over 6 to 10 minutes into the side port of a free-flowing intravenous line followed by flushing with at least 75 to 125 mL of one of the solutions.

Vinorelbine Injection must only be administered intravenously. It is extremely important that the intravenous needle or catheter be properly positioned before any Vinorelbine Injection is injected.

Parenteral drug products should be visually inspected for particulate matter and discoloration prior to administration whenever solution and container permit. If particulate matter is seen, Vinorelbine Injection should not be administered.

Management of Suspected Extravasation

- If Vinorelbine Injection leakage into surrounding tissue occurs or is suspected, immediately stop administration of Vinorelbine Injection and initiate appropriate management measures in accordance with institutional policies [see Warnings and Precautions (5.4)].

2.4 Procedures for Proper Handling and Disposal

Vinorelbine Injection is a cytotoxic drug. Follow applicable special handling and disposal procedures^1.

Exercise caution in handling and preparing the solution of Vinorelbine Injection. The use of gloves is recommended. If the solution of Vinorelbine Injection contacts the skin or mucosa, immediately wash the skin or mucosa thoroughly with soap and water.

Avoid contamination of the eye with Vinorelbine Injection. If exposure occurs, flush the eyes with water immediately and thoroughly.

Discard unused portion.

3 DOSAGE FORMS AND STRENGTHS

Vinorelbine Injection, USP: 1 mL (10 mg per 1 mL) and 5 mL (50 mg per 5 mL) clear colorless to pale yellow solution in single-dose vial.

4 CONTRAINDICATIONS

None

5 WARNINGS AND PRECAUTIONS

5.1 Myelosuppression

Myelosuppression, manifested by neutropenia, anemia and thrombocytopenia, occur in patients receiving vinorelbine as a single agent and in combination with cisplatin [see Adverse Reactions (6.1, 6.2)]. Neutropenia is the major dose-limiting toxicity with vinorelbine. Grade 3-4 neutropenia occurred in 53% of patients treated with vinorelbine at 30 mg/m^2 per week. Dose adjustment due to myelosuppression occurred in 51% of patients (Study 2). In clinical trials with vinorelbine administered at 30 mg/m^2 per week, neutropenia resulted in hospitalizations for pyrexia and/or sepsis in 8% of patients. Death due to sepsis occurred in 1% of patients. Neutropenia nadirs occur between 7 and 10 days after dosing with neutropenia count recovery usually occurring within the following 7 to 14 days.

Monitor complete blood counts prior to each dose of vinorelbine. Do not administer vinorelbine to patients with neutrophil counts <1,000 cells/mm^3. Adjustments in the dosage of vinorelbine should be based on neutrophil counts obtained on the day of treatment [see Dosage and Administration (2.2)].

5.2 Hepatic Toxicity

Drug-induced liver injury manifest by elevated aspartate aminotransferase (AST) and bilirubin occur in patients receiving vinorelbine as a single agent and in combination with cytotoxic agents. Assess hepatic function prior to initiation of vinorelbine and periodically during treatment. Reduce the dose of vinorelbine for patients who develop elevations in total bilirubin ≥ 2 times upper limit of normal [see Dosage and Administration (2.2) and Use in Specific Populations (8.6)].

5.3 Severe Constipation and Bowel Obstruction

Severe and fatal paralytic ileus, constipation, intestinal obstruction, necrosis, and perforation occur in patients receiving vinorelbine. Institute a prophylactic bowel regimen to mitigate potential constipation, bowel obstruction and/or paralytic ileus, considering adequate dietary fiber intake, hydration and routine use of stool softeners.

5.4 Extravasation and Tissue Injury

Extravasation of vinorelbine can result in severe irritation, local tissue necrosis and/or thrombophlebitis. If signs or symptoms of extravasation occur, immediately stop administration of vinorelbine and institute recommended management procedures [see Dosage and Administration (2.2) and Adverse Reactions (6.1)].

5.5 Neurologic Toxicity

Sensory and motor neuropathies, including severe neuropathies, occur in patients receiving vinorelbine. Monitor patients for new or worsening signs and symptoms of neuropathy, such as paresthesia, hyperesthesia, hyporeflexia and muscle weakness while receiving vinorelbine. Discontinue vinorelbine for CTCAE Grade 2 or greater neuropathy [see Dosage and Administration (2.2) and Adverse Reactions (6.1)].

5.6 Pulmonary Toxicity and Respiratory Failure

Pulmonary toxicity, including severe acute bronchospasm, interstitial pneumonitis, acute respiratory distress syndrome (ARDS) occur in patients receiving vinorelbine. Interstitial pneumonitis and ARDS included fatalities. The mean time to onset of interstitial pneumonitis and ARDS after vinorelbine administration was one week (range 3 to 8 days) [see Adverse Reactions (6.1)]. Interrupt vinorelbine in patients who develop unexplained dyspnea or have any evidence of pulmonary toxicity. Permanently discontinue vinorelbine for confirmed interstitial pneumonitis or ARDS.

5.7 Embryo-Fetal Toxicity

Based on findings from animal studies and its mechanism of action, vinorelbine can cause fetal harm when administered to a pregnant woman. In animal reproduction studies in mice and rabbits, embryo and fetal toxicity were observed with administration of vinorelbine at doses approximately 0.33 and 0.18 times the human therapeutic dose, respectively.

Advise pregnant women of the potential risk to a fetus. Advise females of reproductive potential to use effective contraception during treatment with vinorelbine and for 6 months after the final dose. Advise males with female partners of reproductive potential to use effective contraception during treatment with vinorelbine and for 3 months after the final dose [see Use in Specific Populations (8.1, 8.3)].

6 ADVERSE REACTIONS

The following clinically significant adverse reactions are described elsewhere in the labeling:

- Myelosuppression [see Warnings and Precautions (5.1)]
- Hepatic Toxicity [see Warnings and Precautions (5.2)]
- Severe Constipation and Bowel Obstruction [see Warnings and Precautions (5.3)]
- Extravasation and Tissue Injury [see Warnings and Precautions (5.4)]
- Neurologic Toxicity [see Warnings and Precautions (5.5)]
- Pulmonary Toxicity and Respiratory Failure [see Warnings and Precautions (5.6)]

6.1 Clinical Trials Experience

Because clinical trials are conducted under varying designs and in different patient populations, the adverse reaction rates reported in one clinical trial may not be easily compared to those rates reported in another clinical trial and may not reflect the rates actually observed in clinical practice.

Single Agent

The data below reflect exposure to vinorelbine as a single agent administered at a dose of 30 mg/m^2 on a weekly basis to 365 patients enrolled in 3 controlled studies for metastatic NSCLC and advanced breast cancer. The population included 143 patients with previously untreated metastatic NSCLC (Study 3) who received a median of 8 doses of vinorelbine. The patients were aged 32 to 79 (median 61 years), 71% were male, 91% White, 48% had adenocarcinoma histology. The data also reflect exposure to vinorelbine in 222 patients with previously treated advanced breast cancer who received a median of 10 doses of vinorelbine. Vinorelbine is not indicated for the treatment of breast cancer.

Selected adverse reactions reported in these studies are provided in Tables 1 and 2. The most common adverse reactions (≥ 20%) of single agent vinorelbine were leukopenia, neutropenia, anemia, increased aspartate aminotransferase (AST), nausea, vomiting, constipation, asthenia, injection site reaction and peripheral neuropathy. The most common (≥ 5%) Grade 3 or 4 adverse reactions were neutropenia, leukopenia, anemia, increased total bilirubin, increased AST, injection site reaction and asthenia.

Approximately 49% of patients with NSCLC who were treated with vinorelbine experienced at least one dose reduction due to an adverse reaction.

Thirteen percent of patients discontinued vinorelbine due to adverse reactions. The most frequent adverse reactions leading to vinorelbine discontinuation were asthenia, dyspnea, nausea, constipation, anorexia, myasthenia and fever.

Table 1: Hematologic Adverse Reactions Experienced in > 5% of Patients Receiving Vinorelbine*†:
 |  | All Patients (N=365) (%) | NSCLC (N=143) (%)
Laboratory
Hematologic
Neutropenia | < 2,000 cells/mm^3 | 90 | 80
 | < 500 cells/mm^3 | 36 | 29
Leukopenia | < 4,000 cells/mm^3 | 92 | 81
 | < 1,000 cells/mm^3 | 15 | 12
Thrombocytopenia | < 100,000 cells/mm^3 | 5 | 4
Anemia | < 11 g/dl | 83 | 77
 | < 8 g/dl | 9 | 1
Hospitalizations due to neutropenic complications |  | 9 | 8
*Grade based on modified criteria from the National Cancer Institute version 1.
†Patients with NSCLC had not received prior chemotherapy. The majority of the remaining patients had received prior chemotherapy.

Table 2: Non-hematologic Adverse Reactions Experienced in ≥ 5% of Patients Receiving Vinorelbine*†:
 | All Grades |  | Grade 3-4
 | All Patients (%) | NSCLC (%) | All Patients (%) | NSCLC (%)
Laboratory
Hepatic
AST increased (N=346) | 67 | 54 | 6 | 3
Bilirubin increased (N=351) | 13 | 9 | 7 | 5
Clinical
Nausea | 44 | 34 | 2 | 1
Asthenia | 36 | 27 | 7 | 5
Constipation | 35 | 29 | 3 | 2
Injection site reaction | 28 | 38 | 2 | 5
Injection site pain | 16 | 13 | 2 | 1
Neuropathy peripheral‡ | 25 | 20 | <2 | 1
Vomiting | 20 | 15 | 2 | 1
Diarrhea | 17 | 13 | 1 | 1
Alopecia | 12 | 12 | ≤1 | 1
Phlebitis | 7 | 10 | <1 | 1
Dyspnea | 7 | 3 | 3 | 2
*Grade based on modified criteria from the National Cancer Institute version 1.
†Patients with NSCLC had not received prior chemotherapy. The majority of the remaining patients had received prior chemotherapy.
‡ Incidence of paresthesia plus hypesthesia.

Myelosuppression: In clinical trials, Grade 3-4 neutropenia, anemia and thrombocytopenia occurred in 69%, 9% and 1%, respectively of patients receiving single agent vinorelbine. Neutropenia is the major dose-limiting toxicity.

Neurotoxicity: Neurotoxicity was most commonly manifested as constipation, paresthesia, hyperesthesia and hyporeflexia. Grade 3 and 4 neuropathy was observed in 1% of the patients receiving single agent vinorelbine.

Injection Site Reactions: Injection site reactions, including erythema, pain at injection site and vein discoloration, occurred in approximately one third of patients; 5% were severe. Phlebitis (chemical phlebitis) along the vein proximal to the site of injection was reported in 10% of patients.

Cardiovascular Toxicity: Chest pain occurred in 5% of patients; myocardial infarction occurred in ˂0.1% of patients.

Pulmonary Toxicity and Respiratory Failure: Dyspnea (shortness of breath) was reported in 3% of patients; it was severe in 2%. Interstitial pulmonary changes were documented.

Other: Hemorrhagic cystitis and the syndrome of inappropriate ADH secretion were each reported in <1% of patients.

In Combination with Cisplatin

Table 3 presents the incidence of selected adverse reactions, occurring in ≥10% of vinorelbine treated patients reported in a randomized trial comparing the combination of vinorelbine 25 mg/m^2 administered every week of each 28-day cycle and cisplatin 100 mg/m^2 administered on day 1 of each 28-day cycle versus cisplatin alone at the same dose and schedule in patients with previously untreated NSCLC (Study 1).

Patients randomized to vinorelbine plus cisplatin received a median of 3 cycles of treatment and those randomized to cisplatin alone received a median of 2 cycles of treatment. The incidence of Grade 3 and 4 neutropenia was significantly higher in the vinorelbine plus cisplatin arm (82%) compared to the cisplatin alone arm (5%).

Thirty-five percent of the eligible patients in the combination arm required treatment discontinuation due to an adverse reaction compared to 19% in the cisplatin alone arm.

Four patients in the vinorelbine plus cisplatin arm died of neutropenic sepsis. Seven additional deaths were reported in the combination arm: 2 from cardiac ischemia, 1 cerebrovascular accident, 1 multisystem failure due to an overdose of vinorelbine and 3 from febrile neutropenia.

Table 3: Adverse Reactions Experienced by ≥ 10% of Patients on Vinorelbine plus Cisplatin versus Single Agent Cisplatin*
 | Vinorelbine 25mg/m^2 plus Cisplatin 100 mg/m^2 (N=212) |  | Cisplatin 100 mg/m^2 (N=210)
 | All Grades (%) | Grades 3-4 (%) | All Grades (%) | Grades 3-4 (%)
Laboratory
Hematologic
Neutropenia | 89 | 82 | 26 | 5
Anemia | 89 | 24 | 72 | <8
Leukopenia | 88 | 58 | 31 | <1
Thrombocytopenia | 29 | 5 | 21 | <2
Febrile neutropenia† | N/A | 11 | N/A | 0
Renal
Blood creatinine increased | 37 | 4 | 28 | <5
Clinical
Malaise/Fatigue/Lethargy | 67 | 12 | 49 | 8
Vomiting | 60 | 13 | 60 | 14
Nausea | 58 | 14 | 57 | 12
Decreased appetite | 46 | 0 | 37 | 0
Constipation | 35 | 3 | 16 | 1
Alopecia | 34 | 0 | 14 | 0
Weight decreased | 34 | 1 | 21 | <1
Fever without infection | 20 | 2 | 4 | 0
Hearing impaired | 18 | 4 | 18 | <4
Injection site reaction | 17 | <1 | 1 | 0
Diarrhea | 17 | <3 | 11 | <2
Paraesthesia | 17 | <1 | 10 | <1
Taste alterations | 17 | 0 | 15 | 0
Peripheral numbness | 11 | 2 | 7 | <1
Myalgia/Arthralgia | 12 | <1 | 3 | <1
Phlebitis/Thrombosis/Embolism | 10 | 3 | <1 | <1
Weakness | 12 | <3 | 7 | 2
Infection | 11 | <6 | <1 | <1
Respiratory tract infection | 10 | <5 | 3 | 3
*Graded according to the standard SWOG criteria version 1.
†Categorical toxicity grade not specified

Table 4 presents the incidence of selected adverse reactions, occurring in ≥10% of vinorelbine treated patients reported in a randomized trial of vinorelbine plus cisplatin, vindesine plus cisplatin and vinorelbine as a single agent in patients with stage III or IV NSCLC who had not received prior chemotherapy. A total of 604 patients received either vinorelbine 30 mg/m^2 every week plus cisplatin 120 mg/m^2 on Day 1 and Day 29, then every 6 weeks thereafter (N=207), vindesine 3 mg/m^2 for 6 weeks, then every other week thereafter plus cisplatin 120 mg/m^2 on Days 1 and Day 29, then every 6 weeks thereafter (N=193) or vinorelbine 30mg/m^2 every week (N=204).

Patients randomized to vinorelbine plus cisplatin received a median of 15 weeks of treatment, vindesine plus cisplatin 12 weeks and vinorelbine received 13 weeks. Grade 3 and 4 neutropenia was significantly greater in the vinorelbine plus cisplatin arm (78%) compared to vindesine plus cisplatin (48%) and vinorelbine as a single agent (53%). Neurotoxicity, including peripheral neuropathy and constipation, was reported in 44% (Grade 3-4, 7%) of the patients receiving vinorelbine plus cisplatin, 58% (Grade 3-4, 17%) of the patients receiving vindesine and cisplatin and 44% (Grade 3-4, 8.5%) of the patients receiving vinorelbine as a single agent.

Study discontinuation due to an adverse reaction was required in 27, 22 and 10% of the patients randomized to vinorelbine plus cisplatin, vindesine plus cisplatin and cisplatin alone arms, respectively.

Table 4: Adverse Reactions Experienced by ≥ 10 % of Patients from a Comparative Trial of Vinorelbine Plus Cisplatin versus Vindesine Plus Cisplatin versus Single Agent Vinorelbine*
 | Vinorelbine/Cisplatin† |  | Vindesine/Cisplatin‡ |  | Vinorelbine§
 | All Grades (%) | Grades 3-4 (%) | All Grades (%) | Grades 3-4 (%) | All Grades (%) | Grades 3-4 (%)
Laboratory
Hematologic
Neutropenia | 95 | 78 | 79 | 48 | 85 | 53
Leukopenia | 94 | 57 | 82 | 27 | 83 | 32
Thrombocytopenia | 15 | 4 | 10 | 3.5 | 3 | 0
Renal
Blood creatinine increased¦ | 46 | N/A | 37 | N/A | 13 | N/A
Clinical
Nausea/Vomiting | 74 | 30 | 72 | 25 | 31 | 2
Alopecia | 51 | 7.5 | 56 | 14 | 30 | 2
Neurotoxicity¶ | 44 | 7 | 58 | 17 | 44 | 8.5
Diarrhea | 25 | 1.5 | 24 | 1 | 12 | 0.5
Injection site reaction | 17 | 2.5 | 7 | 0 | 22 | 2
Ototoxicity | 10 | 2 | 14 | 1 | 1 | 0
* Grade based on criteria from the World Health Organization (WHO).
† N=194 to 207; all patients receiving vinorelbine/cisplatin with laboratory and non-laboratory data.
‡ N=173 to 192; all patients receiving vindesine/cisplatin with laboratory and non-laboratory data.
§ N=165 to 201; all patients receiving vinorelbine with laboratory and non-laboratory data.
¦ Categorical toxicity grade not specified.
¶ Neurotoxicity includes peripheral neuropathy and constipation.

6.2 Postmarketing Experience

The following adverse reactions have been identified during postapproval use of vinorelbine. Because these reactions are reported voluntarily from a population of uncertain size, it is not always possible to reliably estimate their frequency or establish a causal relationship to drug exposure.

Infections: pneumonia

Immune system disorders: anaphylactic reaction, pruritus, urticaria, angioedema

Nervous system disorders: loss of deep tendon reflexes, muscular weakness, gait disturbance, headache

Ear and labyrinth disorders: vestibular disorder, hearing impaired

Cardiac disorders: tachycardia

Respiratory disorders: pulmonary edema

Vascular disorders: pulmonary embolism, deep vein thrombosis, hypertension, hypotension, flushing, vasodilatation

Gastrointestinal disorders: mucosal inflammation, dysphagia, pancreatitis

Skin disorders: generalized cutaneous reactions (rash), palmar-plantar erythrodysesthesia syndrome

Musculoskeletal and connective tissue disorders: jaw pain, myalgia, arthralgia

General disorders and administration site conditions: injection site rash, urticaria, blistering, sloughing of skin

Injury, poisoning and procedural complications: radiation recall phenomenon, dermatitis, esophagitis

Laboratory abnormalities: electrolyte imbalance including hyponatremia

Other: tumor pain, back pain, abdominal pain

7 DRUG INTERACTIONS

7.1 CYP3A Inhibitors

Exercise caution in patients concurrently taking drugs known to inhibit CYP3A. Concurrent administration of vinorelbine with a CYP3A inhibitor may cause an earlier onset and/or an increased severity of adverse reactions.

8 USE IN SPECIFIC POPULATIONS

8.1 Pregnancy

Risk Summary

Based on findings from animal studies and its mechanism of action [see Clinical Pharmacology (12.1)], vinorelbine can cause fetal harm when administered to a pregnant woman. Available human data are insufficient to inform the drug-associated risk of major birth defects, miscarriage, or adverse maternal or fetal outcomes. In animal reproduction studies in mice and rabbits, embryo and fetal toxicity were observed with administration of vinorelbine at doses approximately 0.33 and 0.18 times the human therapeutic dose, respectively (see Data). Advise pregnant women of the potential risk to a fetus.

In the U.S. general population, the estimated background risk of major birth defects and miscarriage in clinically recognized pregnancies are 2 to 4% and 15 to 20%, respectively.

Data

Animal Data

In a mouse embryo-fetal development study, administration of a single dose of vinorelbine at a dose level of 9 mg/m^2 or greater (approximately 0.33 times the recommended human dose based on body surface area) was embryotoxic and fetotoxic. Vinorelbine was embryotoxic and fetotoxic to pregnant rabbits when administered every 6 days during the period of organogenesis at doses of 5.5 mg/m^2 (approximately 0.18 times the recommended human dose based on body surface area) or greater. At doses that did not cause maternal toxicity in either species, vinorelbine administration resulted in reduced fetal weight and delayed ossification.

8.2 Lactation

Risk Summary

There are no data on the presence of vinorelbine in human milk or its effects on the breastfed infant or on milk production. Because of the potential for serious adverse reactions in breastfed infants from vinorelbine, advise women not to breastfeed during treatment with vinorelbine and for 9 days after the final dose.

8.3 Females and Males of Reproductive Potential

Pregnancy Testing

Verify pregnancy status in females of reproductive potential prior to initiating vinorelbine [see Use in Specific Populations (8.1)].

Contraception

Females

Vinorelbine can cause fetal harm when administered to pregnant women [see Use in Specific Populations (8.1)]. Advise female patients of reproductive potential to use effective contraception during treatment with vinorelbine and for 6 months after the final dose.

Males

Vinorelbine may damage spermatozoa [see Nonclinical Toxicology (13.1)]. Advise males with female sexual partners of reproductive potential to use effective contraception during treatment with vinorelbine and for 3 months after the final dose.

Infertility

Males

Based on animal findings, vinorelbine may impair fertility in males [see Nonclinical Toxicology (13.1)].

8.4 Pediatric Use

The safety and effectiveness of vinorelbine in pediatric patients have not been established.

Results from a single-arm study of vinorelbine administered at the dose of 33.75 mg/m^2 (for 35 patients) or at the dose of 30 mg/m^2 (for 11 patients) every week for 6 weeks followed by 2 weeks of rest were evaluated (courses of 8 weeks). Forty-six patients age 1 to 25 (median 11 years) with recurrent solid malignant tumors, including rhabdomyosarcoma or undifferentiated sarcoma (N=21 patients), neuroblastoma (N= 4 patients) and central nervous system (CNS) tumors (N=21 patients), were enrolled. The most significant grade 3 or 4 hematological adverse reactions were neutropenia (70%) and anemia (33%). The most significant grade 3 or 4 non-hematological adverse reactions were motor (15%) or cranial (13%) neuropathy, hypoxia (13%) and dyspnea (11%). Objective tumor response was observed in 2 out of 21 patients with rhabdomyosarcoma or undifferentiated sarcoma. No objective tumor response was observed in patients with CNS tumors (N=21) or neuroblastoma (N=4).

8.5 Geriatric Use

Of the 769 number of patients who received vinorelbine as a single agent and in combination with cisplatin in studies 1, 2 and 3, 247 patients were 65 years of age or older. No overall differences in safety, efficacy and pharmacokinetic parameters were observed between these patients and younger patients [see Clinical Pharmacology (12.3)].

8.6 Hepatic Impairment

The influence of hepatic impairment on the pharmacokinetics of vinorelbine has not been evaluated, but the liver plays an important role in the metabolism of vinorelbine. Elevated AST occurs in >60% of the patients receiving vinorelbine as a single agent (6% Grade 3-4). Therefore, exercise caution in patients with hepatic impairment. Reduce the dose of vinorelbine for patients with elevated serum total bilirubin concentrations [see Dosage and Administration (2.2) and Warnings and Precautions (5.2)].

10 OVERDOSAGE

There is no known antidote for overdoses of vinorelbine. Overdoses involving quantities up to 10 times the recommended dose (30 mg/m^2) have been reported. The adverse reactions described were consistent with those listed in the ADVERSE REACTIONS section, including paralytic ileus, stomatitis and esophagitis. Bone marrow aplasia, sepsis and paresis have also been reported. Fatalities have occurred following overdose of vinorelbine. If overdosage occurs, general supportive measures together with appropriate blood transfusions, growth factors and antibiotics should be instituted as deemed necessary by the physician.

11 DESCRIPTION

Vinorelbine Injection, USP contains vinorelbine, a semi-synthetic vinca alkaloid. The molecular formula for vinorelbine tartrate is C45H54N4O8•2C4H6O6. It has a molecular weight of 1079.11. The structural formula is as follows:

Vinorelbine tartrate is a white to light yellow amorphous powder. It is easily soluble in water, very soluble in methanol and practically insoluble in hexane.

Vinorelbine Injection, USP is a sterile nonpyrogenic aqueous solution for intravenous use. Each milliliter of solution contains 10 mg vinorelbine (equivalent to 13.85 mg vinorelbine tartrate) in Water for Injection, USP. The pH of Vinorelbine Injection, USP is approximately 3.5.

12 CLINICAL PHARMACOLOGY

12.1 Mechanism of Action

Vinorelbine is a vinca alkaloid that interferes with microtubule assembly. The antitumor activity of vinorelbine is thought to be due primarily to inhibition of mitosis at metaphase through its interaction with tubulin. Vinorelbine may also interfere with: 1) amino acid, cyclic AMP and glutathione metabolism, 2) calmodulin-dependent Ca++-transport ATPase activity, 3) cellular respiration, and 4) nucleic acid and lipid biosynthesis. Vinorelbine inhibited mitotic microtubule formation in intact mouse embryo tectal plates at a concentration of 2 μM inducing a blockade of cells at metaphase, but produced depolymerization of axonal microtubules at a concentration 40 μM, suggesting a modest selectivity of vinorelbine for mitotic microtubules.

12.3 Pharmacokinetics

The pharmacokinetics of vinorelbine were studied in 49 patients who received doses of 30 mg/m^2 administered as 15- to 20-minute constant-rate infusions. Vinorelbine concentrations in plasma decay in a triphasic manner.

Distribution

Steady-state volume of distribution (VSS) values range from 25.4 to 40.1 L/kg. Vinorelbine demonstrated high binding to human platelets and lymphocytes. The free fraction was approximately 0.11 in human plasma over a concentration range of 234 to 1169 ng/mL. The binding to plasma constituents in cancer patients ranged from 79.6% to 91.2%. Vinorelbine binding was not altered in the presence of cisplatin, fluorouracil, or doxorubicin.

Elimination

The terminal phase half-life averages 27.7 to 43.6 hours and the mean plasma clearance ranges from 0.97 to 1.26 L/hr/kg.

Metabolism

Vinorelbine undergoes substantial hepatic elimination in humans, with large amounts recovered in feces. Two metabolites of vinorelbine have been identified in human blood, plasma and urine; vinorelbine N-oxide and deacetylvinorelbine. Deacetylvinorelbine has been demonstrated to be the primary metabolite of vinorelbine in humans and has been shown to possess antitumor activity similar to vinorelbine. Therapeutic doses of vinorelbine (30 mg/m^2) yield very small, if any, quantifiable levels of either metabolite in blood or urine. The metabolism of vinorelbine is mediated by hepatic CYP3A.

Excretion

After intravenous administration of radioactive vinorelbine, approximately 18% and 46% of administered radioactivity was recovered in urine and feces, respectively. In a different study, 10.9% ± 0.7% of a 30 mg/m^2 intravenous dose was excreted as parent drug in urine.

Specific Populations

Age has no effect on the pharmacokinetics (CL, VSS and t1/2) of vinorelbine.

Drug Interaction Studies

The pharmacokinetics of vinorelbine are not influenced by the concurrent administration of cisplatin.

13 NONCLINICAL TOXICOLOGY

13.1 Carcinogenesis, Mutagenesis, Impairment of Fertility

The carcinogenic potential of vinorelbine has not been studied. Vinorelbine has been shown to affect chromosome number and possibly structure in vivo (polyploidy in bone marrow cells from Chinese hamsters and a positive micronucleus test in mice). It was not mutagenic in the Ames test and gave inconclusive results in the mouse lymphoma TK Locus assay.

Vinorelbine did not affect fertility to a statistically significant extent when administered to rats on either a once-weekly (9 mg/m^2, approximately one third the human dose) or alternate-day schedule (4.2 mg/m^2, approximately 0.14 times the human recommended dose) prior to and during mating. In male rats, administration of vinorelbine twice weekly for 13 or 26 weeks at dose levels of 2.1 and 7.2 mg/m^2 (approximately 0.07 and 0.24 times the recommended human dose), respectively, resulted in decreased spermatogenesis and prostate/seminal vesicle secretion.

14 CLINICAL STUDIES

14.1 Combination Use with Cisplatin

The safety and efficacy of vinorelbine in combination with cisplatin was evaluated in two randomized, multicenter trials.

Cisplatin 100mg/m^2

Study 1 was a randomized, multicenter, open-label trial of vinorelbine plus cisplatin and cisplatin alone for the treatment of stage IV or stage IIIb NSCLC in patients with malignant pleural effusion or multiple lesions in more than one lobe of the ipsilateral lung who had not received prior chemotherapy. A total of 432 patients were randomized 1:1 to receive either vinorelbine 25 mg/m^2 on Day 1 then every week of each 28-day cycle plus cisplatin 100 mg/m^2 administered on Day 1 of each 28-day cycle (N=214) or single agent cisplatin 100 mg/m^2 on Day 1 of each 28-day cycle (N=218).

Patient demographics and disease characteristics were similar between arms. Of the overall study population, the median age was 64 (range 33 to 84), 66% were male, 80% were White, 92% had stage IV disease and 8% stage IIIB, 53% had adenocarcinoma, 21% squamous cell, 14% large cell histology. The major efficacy outcome measure was overall survival. The efficacy results are presented in Table 7 and Figure 1.

Table 7. Efficacy Results (Study 1)
 | Vinorelbine plus Cisplatin (N=214) | Cisplatin (N=218)
Overall Survival
Median Survival in months (95% CI) | 7.8 (6.9, 9.6) | 6.2 (5.4, 7.7)
Unstratified log-rank p-value | 0.01
Overall Response rate (ORR)
Evaluable patients ORR (95% CI) | N=206 19% (14%, 25%) | N=209 8% (5%, 13%)
Chi-square test p-value | <0.001

Figure 1: Overall Survival Vinorelbine / Cisplatin versus Single Agent Cisplatin

Cisplatin 120mg/m^2

Study 2 was a randomized, 3-arm, open-label, multicenter trial of vinorelbine plus cisplatin, vindesine plus cisplatin and vinorelbine as a single agent for the treatment of patients with stage III or IV NSCLC who had not received prior chemotherapy. The study was conducted in Europe. A total of 612 patients were randomized 1:1:1 to receive vinorelbine 30 mg/m^2 every week of a 6-week cycle plus cisplatin 120 mg/m^2 on Day 1 and Day 29, then every 6 weeks thereafter (N=206); and vindesine 3 mg/m^2 for 6 weeks, then every other week thereafter plus cisplatin 120 mg/m^2 on Days 1 and Day 29, then every 6 weeks thereafter (N=200) or vinorelbine 30mg/m^2 every week of a 6-week cycle (N=206). The main efficacy outcome measure was to compare overall survival between vinorelbine plus cisplatin and vindesine plus cisplatin. The other efficacy outcome measure was to compare overall survival in the better of the two combination regimens to that of vinorelbine as a single agent.

Patient demographics were in general similar between arms: the median age of the overall population was 60 years (range 30 to 75), 90% were male, 78% had WHO performance status of 0 or 1. Tumor characteristics were in general similar with the exception of histologic subtype of NSCLC. Adenocarcinoma was the histologic subtype in 32% of patients in the vinorelbine plus cisplatin arm, 40% of patients in vindesine plus cisplatin arm and 28% of patients on the vinorelbine arm. Ten percent of the patients had stage IIIA disease, 28% stage IIIB and 50% stage IV. Twelve percent of the patients had received prior surgery or radiotherapy.

The efficacy results of Study 2 are presented in Table 8.

Table 8. Efficacy Results (Study 2)
 | Vinorelbine (N=206) | Vinorelbine plus cisplatin (N=206) | Vindesine plus cisplatin (N=200)
Median survival in months (99.5% CI) | 7.2 (5.4, 9.1) | 9.2 (7.4, 11.1) | 7.4 (6.1, 9.1)
Unstratified log-rank p-value | n/a^1 | 0.087
Unstratified log-rank p-value | 0.05 |  | n/a
Overall Response (ORR) Evaluable Patients ORR (95% CI) | N=205 14% (10%, 20%) | N=203 28% (22%, 35%) | N=198 19% (14%, 25%)
Chi-square test p-value | n/a | 0.03
Chi-square test p-value | < 0.001 |  | n/a
^1n/a = not applicable

14.2 Single Agent

The safety and efficacy of vinorelbine as a single agent was evaluated in one randomized multicenter trial. Study 3 was a randomized, open-label clinical trial of vinorelbine or fluorouracil (FU) plus leucovorin (LV) in patients with Stage IV NSCLC who had not received prior chemotherapy. A total of 211 patients were randomized 2:1 to receive vinorelbine 30 mg/m^2 weekly of an 8-week cycle (N=143) or FU 425 mg/m^2 bolus intravenously plus LV 20 mg/m^2 bolus intravenously daily for 5 days of a 4-weeks cycle (N=68).

Patient demographics and disease characteristics were in general similar between arms. In the overall population, the median age was 61 years (range 32 to 83), 74% were male, 88% were White, 46% had adenocarcinoma histology. Fifty percent of the patients had Karnofsky performance status ≥ 90 in the vinorelbine arm compared to 38% in the FU/LV arm.

The primary efficacy outcome of the study was overall survival. The median survival time was 30 weeks versus 22 weeks for patients receiving vinorelbine versus FU/LV, respectively (p=0.06). Partial objective responses were observed in 11.1% (95% CI=6.2%, 17.9%) and 3.5% (95% CI=0.4%, 11.9%) of patients who received vinorelbine and FU/LV, respectively.

15 REFERENCES

1. OSHA. http://www.osha.gov/SLTC/hazardousdrugs/index.html

16 HOW SUPPLIED/STORAGE AND HANDLING

Vinorelbine Injection, USP is supplied as follows:

 | Vinorelbine Injection, USP
NDC | (10 mg per mL) | Package Factor
25021-204-01 | 10 mg per mL Single-Dose Vial | 1 vial per carton
25021-204-05 | 50 mg per 5 mL Single-Dose Vial | 1 vial per carton

Vinorelbine Injection, USP is a clear, colorless to pale yellow aqueous solution.

Storage Conditions
Store refrigerated between 2° and 8°C (36° and 46°F).

Do not freeze.
Protect from light. Retain in carton until time of use.
Discard unused portion.

Unopened vials of Vinorelbine Injection, USP are stable at 25°C (77°F) for up to 72 hours. Store diluted solutions of Vinorelbine Injection, USP at 5° to 30°C (41° to 86°F) [see Dosage and Administration (2.3)].

Vinorelbine Injection, USP is a cytotoxic drug. Follow applicable special handling and disposal procedures.^1

Sterile, Nonpyrogenic, Preservative-free.
The container closure is not made with natural rubber latex.

17 PATIENT COUNSELING INFORMATION

Myelosuppression

Advise patients to contact a healthcare provider for new onset fever, or symptoms of infection [see Warnings and Precautions (5.1)].

Constipation and Bowel Obstruction

Advise patients to follow a diet rich in fibers, drink fluids to stay well hydrated and use stool softeners to avoid constipation. Contact a health care provider for severe constipation, new onset abdominal pain, nausea and vomiting [see Warnings and Precautions (5.3)].

Neurologic Toxicity

Advise patients to contact a health care provider for new onset or worsening of numbness, tingling, decrease sensation or muscle weakness [see Warnings and Precautions (5.5)].

Pulmonary Toxicity

Advise patients to contact a healthcare provider for new onset or worsening of shortness of breath, cough, wheezing or other new pulmonary symptoms [see Warnings and Precautions (5.6)].

Embryo-Fetal Toxicity

- Advise pregnant women of the potential risk to a fetus. Advise females to inform their healthcare provider of a known or suspected pregnancy [see Warnings and Precautions (5.7) and Use in Specific Populations (8.1, 8.3)].
- Advise females of reproductive potential to use effective contraception during treatment with Vinorelbine Injection and for 6 months after the final dose [see Use in Specific Populations (8.3)].
- Advise males with female partners of reproductive potential to use effective contraception during treatment with Vinorelbine Injection and for 3 months after the final dose [see Use in Specific Populations (8.3) and Nonclinical Toxicology (13.1)].

Lactation

Advise women not to breastfeed during treatment with Vinorelbine Injection and for 9 days after the final dose [see Use in Specific Populations (8.2)].

Infertility

Advise males of reproductive potential that Vinorelbine Injection may impair fertility [see Use in Specific Populations (8.3)].

SAGENT®
Mfd. for SAGENT Pharmaceuticals
Schaumburg, IL 60195 (USA)
Made in China
©2023 Sagent Pharmaceuticals

Revised: September 2023

SAGENT Pharmaceuticals®

PACKAGE LABEL – PRINCIPAL DISPLAY PANEL – Vial Label

NDC 25021-204-01

VINORELBINE INJECTION, USP

10 mg per mL

Rx only

1 mL Single-Dose Vial

Must Be Diluted

For Intravenous Use Only

Caution: Cytotoxic Agent

PACKAGE LABEL – PRINCIPAL DISPLAY PANEL – Vial Label

NDC 25021-204-05

VINORELBINE INJECTION, USP

50 mg per 5 mL

(10 mg per mL)

Rx only

5 mL Single-Dose Vial

Must Be Diluted

For Intravenous Use Only

Caution: Cytotoxic Agent